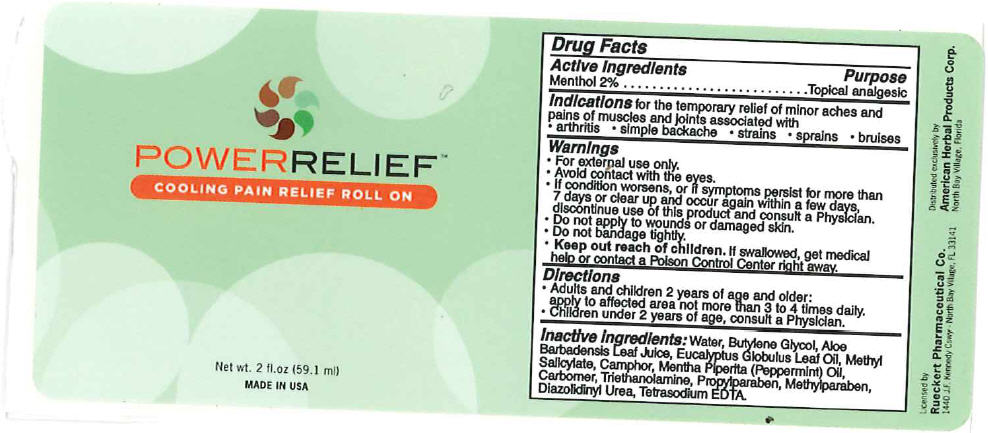 DRUG LABEL: Power Relief
NDC: 64483-007 | Form: GEL
Manufacturer: Clientele, Inc.
Category: otc | Type: HUMAN OTC DRUG LABEL
Date: 20110906

ACTIVE INGREDIENTS: Menthol 2 mL/100 mL
INACTIVE INGREDIENTS: Camphor (Synthetic) 0.52 mL/100 mL; Water 84.61 mL/100 mL; Eucalyptus oil 0.81 mL/100 mL

POWERRELIEF™
COOLING PAIN RELIEF ROLL ON

Drug Facts

Active Ingredients

Menthol 2%

Purpose

Topical analgesic

Indications

for the temporary relief of minor aches and pains of muscles and joints associated with

- arthritis
- simple backache
- strains
- sprains
- bruises

Warnings

- For external use only.

WHEN USING

- Avoid contact with the eyes.

ASK DOCTOR

- If condition worsens, or if symptoms persist for more than 7 days or clear up and occur again within a few days, discontinue use of this product and consult a Physician.

- Do not apply to wounds or damaged skin.
- Do not bandage tightly.

KEEP OUT OF REACH OF CHILDREN

- Keep out reach of children. If swallowed, get medical help or contact a Poison Control Center right away.

Directions

- Adults and children 2 years of age and older:
  apply to affected area not more than 3 to 4 times daily.
- Children under 2 years of age, consult a Physician.

Inactive Ingredients

Water, Butylene Glycol, Aloe Barbadensis Leaf Juice, Eucalyptus Globulus Leaf Oil, Methyl Salicylate, Camphor, Mentha Piperita (Peppermint) Oil, Carbomer, Triethanolamine, Propylparaben, Methylparaben, Diazolidinyl Urea, Tetrasodium EDTA.

Distributed exclusively by
American Herbal Products Corp.
North Bay Village, Florida

PRINCIPAL DISPLAY PANEL - 59.1 ml Bottle Label

POWERRELIEF™
COOLING PAIN RELIEF ROLL ON

Net wt. 2 fl.oz (59.1 ml)
MADE IN USA